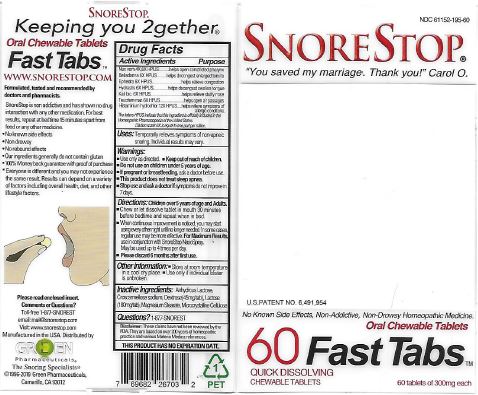 DRUG LABEL: SnoreStop 60 FastTabs
NDC: 61152-195 | Form: TABLET, CHEWABLE
Manufacturer: Green Pharmaceuticals Inc
Category: homeopathic | Type: HUMAN OTC DRUG LABEL
Date: 20221014

ACTIVE INGREDIENTS: ATROPA BELLADONNA 6 [hp_X]/30 1; EPHEDRA DISTACHYA FLOWERING TWIG 6 [hp_X]/30 1; HISTAMINE DIHYDROCHLORIDE 12 [hp_X]/30 1; GOLDENSEAL 6 [hp_X]/30 1; POTASSIUM DICHROMATE 6 [hp_X]/30 1; STRYCHNOS NUX-VOMICA SEED 6 [hp_X]/30 1; TEUCRIUM MARUM 6 [hp_X]/30 1
INACTIVE INGREDIENTS: ANHYDROUS LACTOSE; CROSCARMELLOSE SODIUM; DEXTROSE; LACTOSE; MAGNESIUM STEARATE; CELLULOSE, MICROCRYSTALLINE

SnoreStop 60 FastTabs

Ingredients (HPUS):

Belladonna 6X, Ephedra vulg. 6X, Histaminum hydrochlorinum 12X, Hydrastatis 6X, Kali bic. 6X, Nux vom. 4X, 6X, Teucrium mar. 6X.

Inactive Ingredients:

Anhydrous Lactose, Croscarmellose sodium, Dextrose (45mg/tab), Lactose (180mg/tab), Magnesium Stearate, Microcrystalline Cellulose.

Uses:

Temporarily relieves symptoms of non-apneic snoring. Individual results may vary.

Warnings:

Use only as directed. Keep out of reach of children. Do not use on children under 5 years of age. If pregnant or breastfeeding, ask a doctor before use. This product does not treat sleep apnea. Stop use and ask a doctor if symptoms do not improve in 7 days.

Indications & Usage:

Chew or suck one tablet 30 minutes before bedtime and repeat at bedtime. When continuous improvement is noticed, you may start using every other night until no longer needed. In some cases, regular use may be more effective. For Maximum Results, use in conjunction with SnoreStop Naso Spray. May be used up to 4 times per day. Please discard 6 months after first use.

Keep out of reach of children.

Other information:

- Store at room temperature in a cool dry place.
- Use only if individual blister is unbroken.

Questions?

1-877-SNOREST

Directions: Children over 5 years of age and Adults

Chew or suck one tablet 30 minutes before bedtime and repeat at bedtime. When continuous improvement is noticed, you may start using every other night until no longer needed. In some cases, regular use may be more effective. For Maximum Results, use in conjunction with SnoreStop Naso Spray. May be used up to 4 times per day. Please discard 6 months after first use.